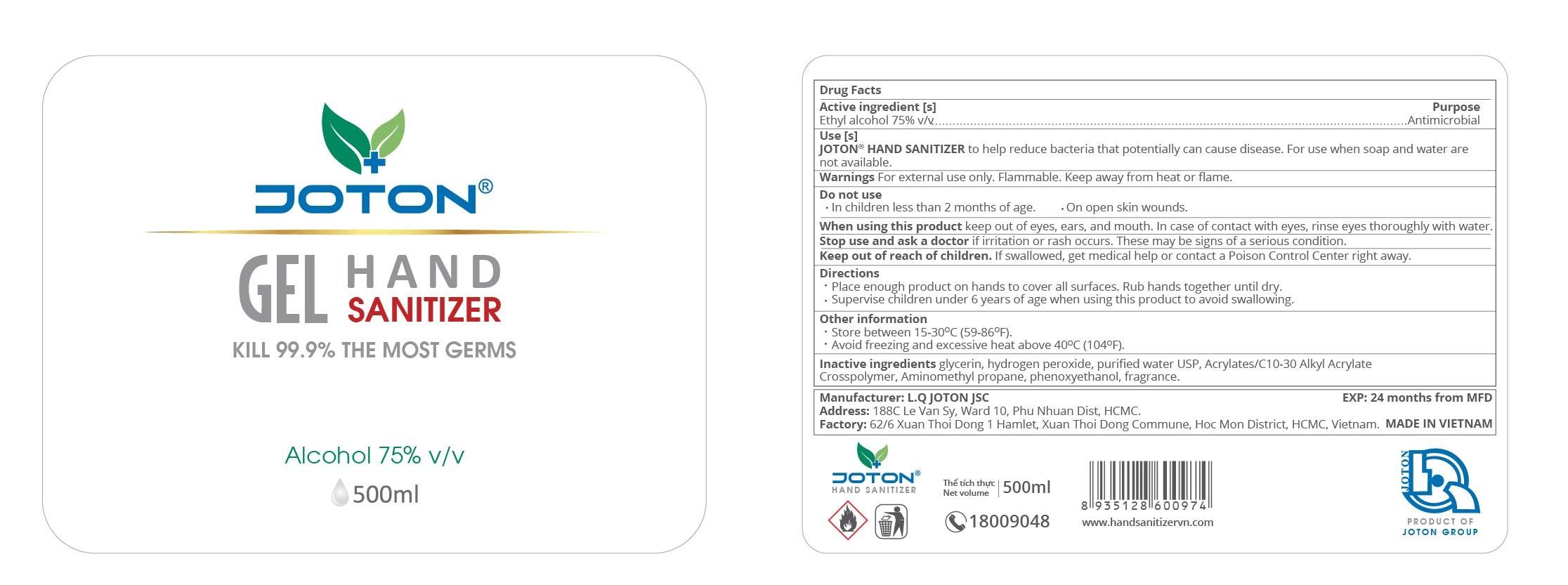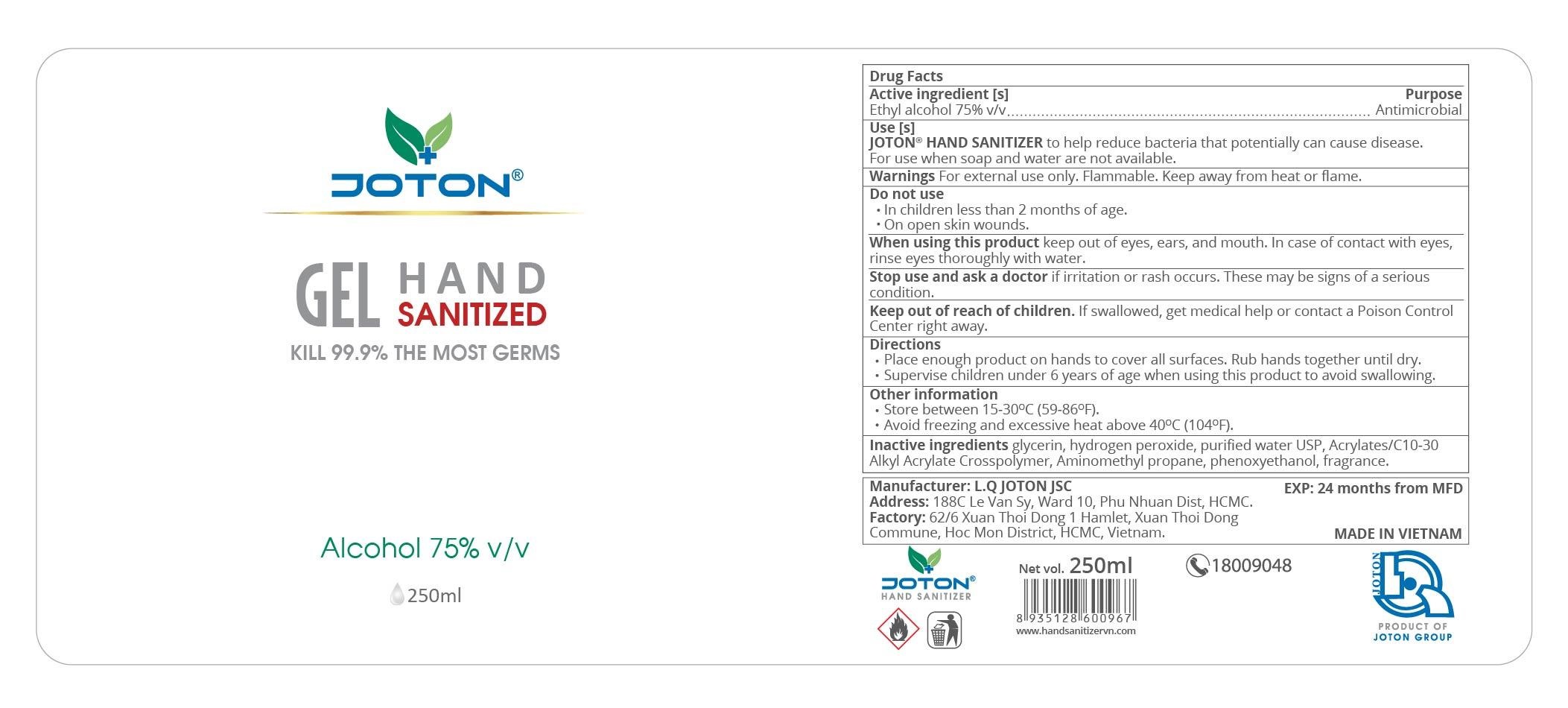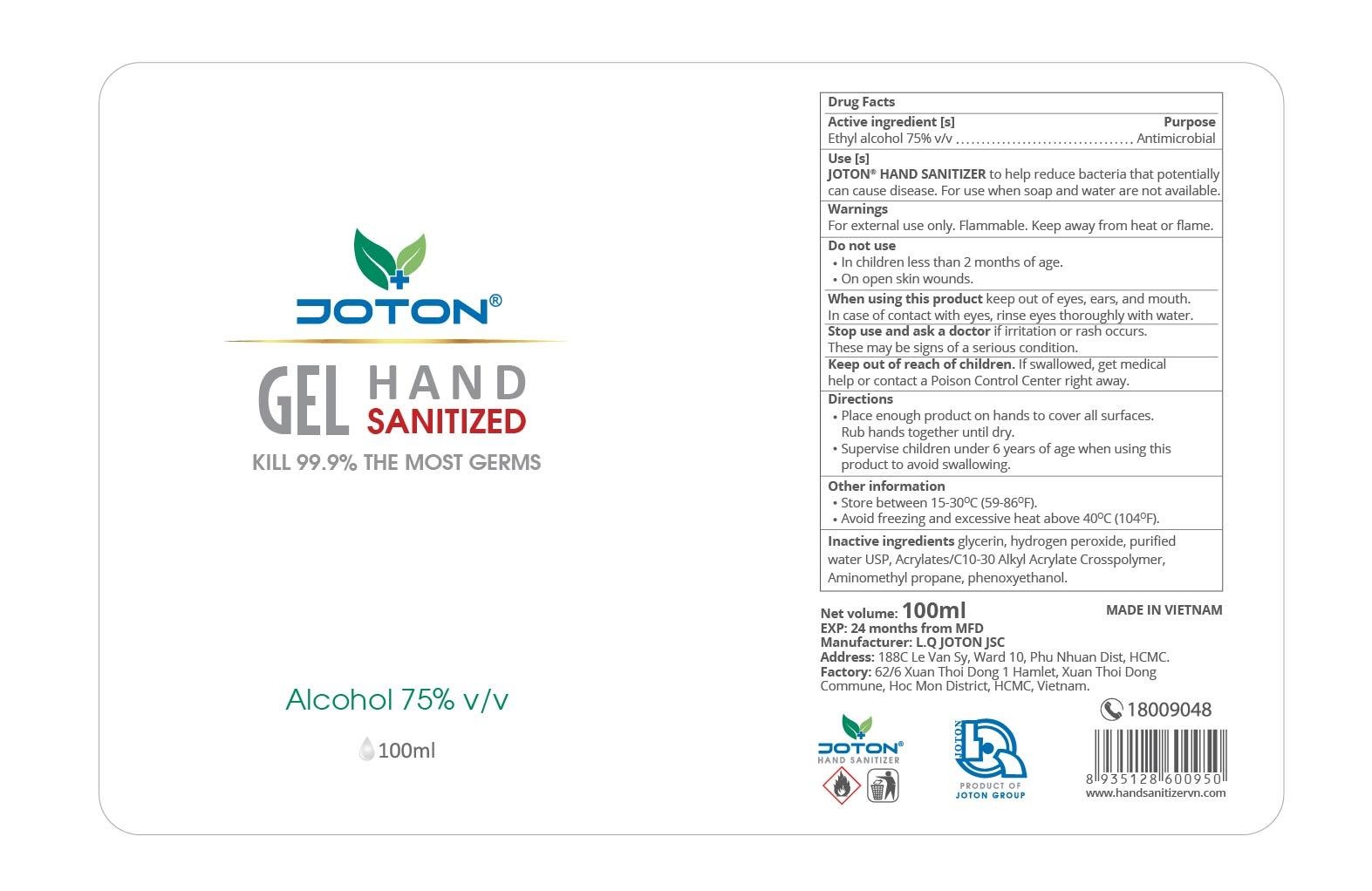 DRUG LABEL: Joton Hand Sanitizer Gel
NDC: 77078-001 | Form: GEL
Manufacturer: L.Q JOTON JOINT STOCK COMPANY- PAINT MANUFACTURING FACTORY
Category: otc | Type: HUMAN OTC DRUG LABEL
Date: 20200818

ACTIVE INGREDIENTS: ALCOHOL 0.75 mL/1 mL
INACTIVE INGREDIENTS: GLYCERIN; HYDROGEN PEROXIDE; WATER; CARBOMER INTERPOLYMER TYPE A (ALLYL SUCROSE CROSSLINKED); AMINOMETHYLPROPANOL; PHENOXYETHANOL

Pasion Alcohol Wet Wipes

Active ingredient [s]

Ethyl alcohol 75% v/v

Purpose

Antimicrobial

Use [s]

JOTON HAND SANITIZER to help reduce bacteria that potentially can cause disease. For use when soap and water are not available.

Warnings

For external use only. Flammable. Keep away from heat or flame.

Do not use

- In children less than 2 months of age.
- On open skin wounds.

When using this product

keep out of eyes, ears, and mouth. In case of contact with eyes, rinse eyes thoroughly with water.

Stop use and ask a doctor

if irritation or rash occurs. These may be signs of a serious condition.

Keep out of reach of children.

If swallowed, get medical help or contact a Poison Control Center right away.

Directions

- Place enough product on hands to cover all surfaces. Rub hands together until dry.
- Supervise children under 6 years of age when using this product to avoid swallowing.

Other information

- Store between 15-30°C (59-86°F).
- Avoid freezing and excessive heat above 40°C (104°F).

Inactive ingredients

glycerin, hydrogen peroxide, purified water USP, Acrylates/C10-30 Alkyl Acrylate Crosspolymer, Aminomethyl Propanol, phenoxyethanol.